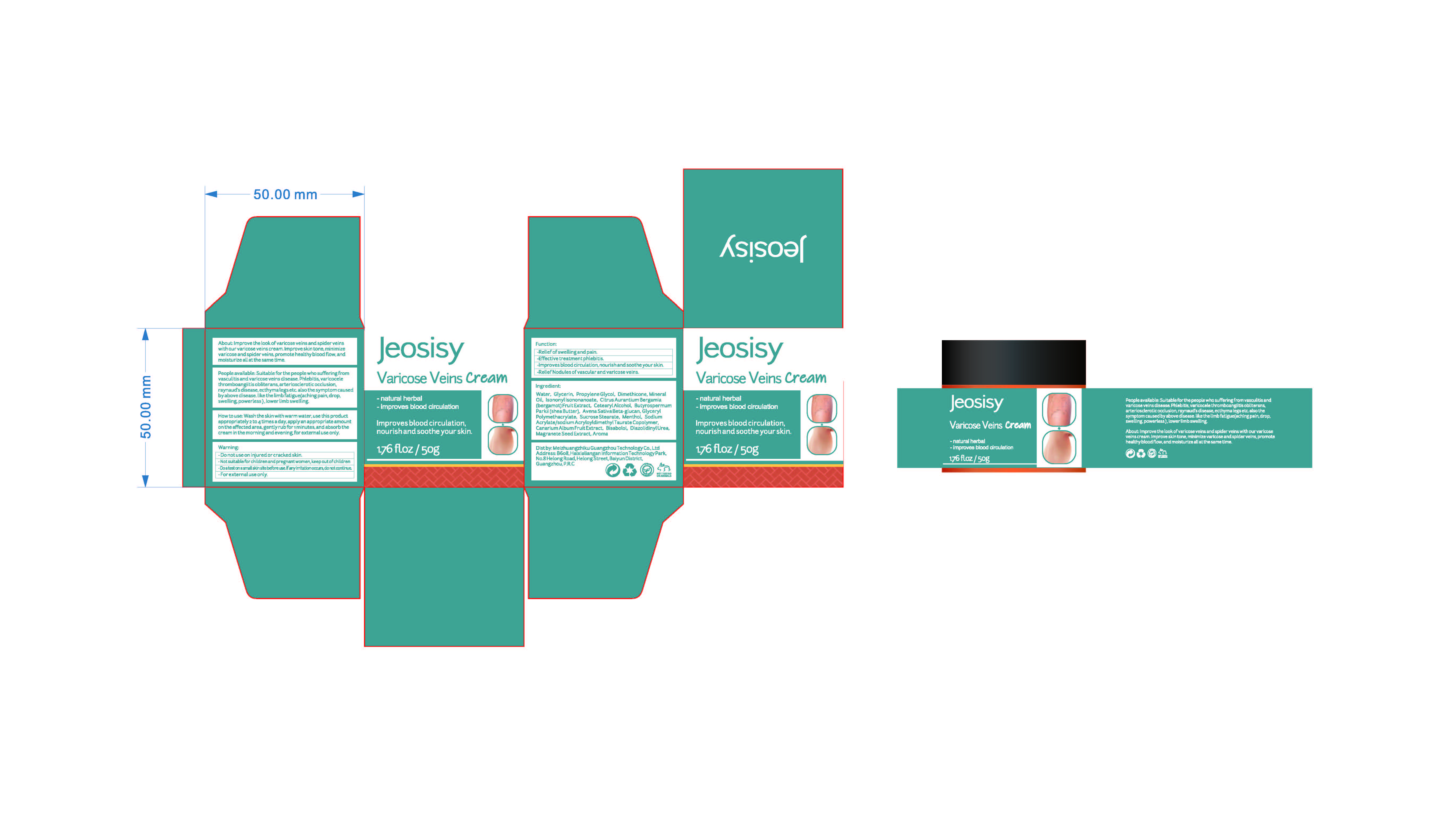 DRUG LABEL: Varicose Veins Cream
NDC: 83782-101 | Form: CREAM
Manufacturer: Meizhuangzhiku Guangzhou Technology Co.,Ltd
Category: otc | Type: HUMAN OTC DRUG LABEL
Date: 20231101

ACTIVE INGREDIENTS: AESCULUS CHINENSIS WHOLE 0.1 g/100 g; MENTHOL 0.2 g/100 g; AMMOPIPTANTHUS MONGOLICUS STEM 0.1 g/100 g
INACTIVE INGREDIENTS: CHINESE CINNAMON OIL; MINERAL OIL; GLYCERYL POLYMETHACRYLATE (300000 MPA.S); SHEA BUTTER; ANGELICA ROOT OIL; LEVOMENOL; PENTYLENE GLYCOL; BERGAMOT OIL; OAT BRAN; PROPYLENE GLYCOL; GLYCERIN; ISONONYL ISONONANOATE; BLACK OLIVE; DIAZOLIDINYL UREA; PRUNUS PERSICA FLOWER; REHMANNIA GLUTINOSA ROOT; WATER; ESCIN; SUCROSE STEARATE; DIMETHICONE; CETOSTEARYL ALCOHOL; PUNICA GRANATUM SEED; SODIUM ACRYLATE/SODIUM ACRYLOYLDIMETHYLTAURATE COPOLYMER (4000000 MW)

Varicose Veins Cream

Varicose Veins Cream

ACTIVE INGREDIENT

MENTHOL L7T10EIP3A 0.2%
AESCULUS CHINENSIS EXTRACT PGU072XJ6U 0.1%
AMMOPIPTANTHUS MONGOLICUS EXTRACT 2928MM8X42 0.1%

PURPOSE

natural herbal

improves blood circulation

lmproves blood circulation, nourish and soothe your skin

INDICATIONS AND USAGE

People available: Suitable for the people who sufferingfromvasculitis and varicose veins disease.phlebitis,varicocelethromboangiitis obliterans,arteriosclerotic occlusion.raynaud's disease,ecthyma legs etc.also the symptom causedby above disease.like the limb fatigue(aching pain, drop,swelling,powerless),lower limb swelling

Warning:
-Do not use on injured or cracked skin.-Not suitable for children and pregnant women, keep out of children-Doatest on asmall skin site before use.lf anyirritation occurs,do not continue.-For externaluse only.

-Do not use on injured or cracked skin.-Not suitable for children and pregnant women, keep out of children-Doatest on asmall skin site before use.lf anyirritation occurs,do not continue.-For externaluse only.

WHEN USING

Howto use: Wash the skin with warm water, use this productappropriately 2 to 4times a day,applyan appropriate amounton the affected area, gently rub for 1minutes, and absorb thecream in the morning and evening,for externaluse only

STOP USE

If allergic reactions occur during use, please stop using immediately and seek medical assistance.

KEEP OUT OF REACH OF CHILDREN

Not suitable for children and pregnant women, keep out of children

DOSAGE AND ADMINISTRATION

Howto use: Wash the skin with warm water, use this productappropriately 2 to 4 times a day,apply an appropriate amounton the affected area, gently rub for 1minutes, and absorb thecream in the morning and evening,for externaluse only

STORAGE AND HANDLING

Indoor, dark, and stored at room temperature.

INACTIVE INGREDIENT

ESCIN
CHINESE CINNAMON OIL
ANGELICA ARCHANGELICA ROOT OIL
REHMANNIA GLUTINOSA ROOT EXTRACT
WATER
GLYCERIN
PROPYLENE GLYCOL
DIMETHICONE
MINERAL OIL
ISONONYL ISONONANOATE
CITRUS AURANTIUM BERGAMIA
(BERGAMOT)FRUIT EXTRACT
CETEARYL ALCOHOL
PUNICA GRANATUM SEED EXTRACT
BUTYROSPERMUM
PARKII(SHEA BUTTER)
AVENA SATIVA BETA-GLUCAN
GLYCERYL
POLYMETHACRYLATE
SUCROSE STEARATE
SODIUM
ACRYLATE/SODIUM ACRYLOYLDIMETHYL TAURATE COPOLYMER
OLEA EUROPAEA (OLIVE) FRUIT EXTRACT
BISABOLOL
PENTYLENE GLYCOL
DIAZOLIDINYLUREA
AROMA（PRUNUS PERSICA FLOWER）